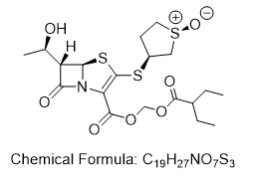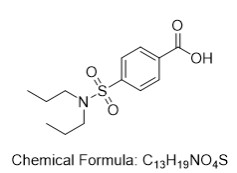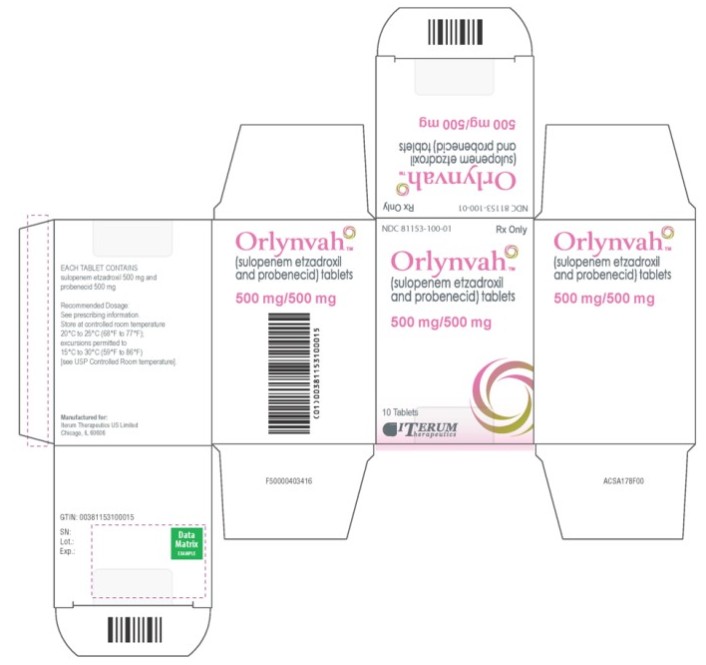 DRUG LABEL: ORLYNVAH
NDC: 81153-100 | Form: TABLET, FILM COATED
Manufacturer: ITERUM THERAPEUTICS US LIMITED
Category: prescription | Type: HUMAN PRESCRIPTION DRUG LABEL
Date: 20251206

ACTIVE INGREDIENTS: SULOPENEM ETZADROXIL 500 mg/1 1; PROBENECID 500 mg/1 1
INACTIVE INGREDIENTS: CROSCARMELLOSE SODIUM; HYDROXYPROPYL CELLULOSE, UNSPECIFIED; LACTOSE MONOHYDRATE; MAGNESIUM STEARATE; MICROCRYSTALLINE CELLULOSE; COCHINEAL; LECITHIN, SOYBEAN; POLYVINYL ALCOHOL; TALC; TITANIUM DIOXIDE; XANTHAN GUM; ALUMINUM HYDROXIDE

HIGHLIGHTS OF PRESCRIBING INFORMATION

These highlights do not include all the information needed to use ORLYNVAHTM safely and effectively. See full prescribing information for ORLYNVAHTM.
ORLYNVAHTM (sulopenem etzadroxil and probenecid) tablets, for oral use
Initial U.S. Approval: 2024

RECENT MAJOR CHANGES

Contraindications, (4) | Removed 12/2025
Warnings and Precautions, Uric Acid Nephropathy in Patients at Risk for Tumor Lysis Syndrome (5.5) | 12/2025

1 INDICATIONS AND USAGE

ORLYNVAH, a combination of sulopenem etzadroxil, a penem antibacterial, and probenecid, a renal tubular transport inhibitor, is indicated for the treatment of uncomplicated urinary tract infections (uUTI) caused by the designated microorganisms Escherichia coli, Klebsiella pneumoniae, or Proteus mirabilis in adult women who have limited or no alternative oral antibacterial treatment options. (1.1)

Limitations of Use

ORLYNVAH is not indicated for the treatment of:

- Complicated urinary tract infections (cUTI) or as step-down treatment after intravenous antibacterial treatment of cUTI. (1.1, 14.2)
- Complicated intra-abdominal infections (cIAI) or as step-down treatment after intravenous antibacterial treatment of cIAI. (1.1, 14.3)

Usage to Reduce Development of Drug-Resistant Bacteria

To reduce the development of drug-resistant bacteria and maintain the effectiveness of ORLYNVAH and other antibacterial drugs, ORLYNVAH should be used only to treat uUTI that are proven or strongly suspected to be caused by susceptible bacteria. Culture and susceptibility information should be utilized in selecting or modifying antibacterial therapy. (1.2, 5.5)

2 DOSAGE AND ADMINISTRATION

- The recommended dosage of ORLYNVAH is one tablet orally twice daily for 5 days. (2.1)
- Administration of ORLYNVAH with food is recommended. (2.1)

3 DOSAGE FORMS AND STRENGTHS

- ORLYNVAH Tablets: 500 mg sulopenem etzadroxil and 500 mg probenecid. (3)

4 CONTRAINDICATIONS

- Patients with a history of hypersensitivity to the components of ORLYNVAH (sulopenem etzadroxil and probenecid) or other beta- lactam antibacterial drugs. (4)
- Patients with known uric acid kidney stones. (4)
- Concomitant use of ORLYNVAH and ketorolac tromethamine is contraindicated. (4)

5 WARNINGS AND PRECAUTIONS

- Hypersensitivity Reactions: Hypersensitivity reactions have been reported in patients treated with ORLYNVAH. Serious and occasionally fatal hypersensitivity reactions, including anaphylaxis, have been reported with beta-lactam antibacterial drugs. Severe allergic reactions and anaphylaxis have been reported with the use of probenecid (a component of ORLYNVAH). If an allergic reaction to ORLYNVAH occurs, discontinue the drug and institute appropriate therapy. (5.1)
- Clostridioides difficile-Associated Diarrhea (CDAD): This has been reported with nearly all systemic antibacterial agents. Evaluate if diarrhea occurs. (5.2)
- Exacerbation of Gout: When prescribing ORLYNVAH to patients with a known history of gout, ensure appropriate therapy of gout is instituted. (5.4)
- Uric Acid Nephropathy in Patients at Risk for Tumor Lysis Syndrome: When prescribing ORLYNVAH to patients with risk factors for tumor lysis syndrome, take appropriate measures to reduce the risk. (5.5)

6 ADVERSE REACTIONS

The most common adverse reactions (≥2%) in patients treated with ORLYNVAH were diarrhea, nausea, vulvovaginal mycotic infection, headache, and vomiting. (6.1)

To report SUSPECTED ADVERSE REACTIONS, contact Iterum Therapeutics at 1-866-414-SULO or FDA at 1-800-FDA-1088 or www.fda.gov/medwatch.

7 DRUG INTERACTIONS

- Ketoprofen: Concomitant use is not recommended (7.1)
- See full prescribing information for additional clinically significant drug interactions with ORLYNVAH (7.1)

FULL PRESCRIBING INFORMATION

1 INDICATIONS AND USAGE

1.1 Uncomplicated Urinary Tract Infections

ORLYNVAH is indicated for the treatment of uncomplicated urinary tract infections (uUTI) caused by the designated microorganisms Escherichia coli, Klebsiella pneumoniae, or Proteus mirabilis in adult women who have limited or no alternative oral antibacterial treatment options.

Limitations of Use

ORLYNVAH is not indicated for the treatment of:

- Complicated urinary tract infections (cUTI) or as step-down treatment after intravenous antibacterial treatment of cUTI [see Clinical Studies (14.2)].
- Complicated intra-abdominal infections (cIAI)) or as step-down treatment after intravenous antibacterial treatment of cIAI [see Clinical Studies (14.3)].

1.2 Usage to Reduce Development of Drug-Resistant Bacteria

To reduce the development of drug-resistant bacteria and maintain the effectiveness of ORLYNVAH and other antibacterial drugs, ORLYNVAH should be used only to treat uUTI that are proven or strongly suspected to be caused by susceptible bacteria. Culture and susceptibility information should be utilized in selecting or modifying antibacterial therapy [see Warnings and Precautions (5.5)].

2 DOSAGE AND ADMINISTRATION

2.1 Recommended Dosage

The recommended dosage of ORLYNVAH is one tablet (sulopenem etzadroxil 500 mg and probenecid 500 mg) orally twice daily for 5 days. Administration of ORLYNVAH with food is recommended [see Clinical Pharmacology (12.3)].

2.2 Recommended Dosage in Patients with Renal Impairment

Administration of ORLYNVAH is not recommended in patients with creatinine clearance (CrCL) less than 15 mL/min or patients on hemodialysis. No dosage adjustment is required for ORLYNVAH in patients with CrCL greater than or equal to15 mL/min [see Use in Specific Populations (8.6) and Clinical Pharmacology (12.3)].

2.3 Recommendations Regarding Missed Dose(s)

If a dose of ORLYNVAH is missed, instruct patients to take the dose as soon as possible. Do not double the dose to make up for the missed dose.

3 DOSAGE FORMS AND STRENGTHS

ORLYNVAH (sulopenem etzadroxil 500 mg and probenecid 500 mg) tablets are supplied as pink, oval-shaped, film-coated, fixed-dose, bilayer combination tablets debossed with SULO on one side and plain on the other side.

4 CONTRAINDICATIONS

ORLYNVAH is contraindicated in patients with:

• A history of hypersensitivity to the components of ORLYNVAH (sulopenem etzadroxil and probenecid) or other beta-lactam antibacterial drugs [see Warnings and Precautions (5.1)]

• Known uric acid kidney stones [see Warnings and Precautions (5.3)]

Concomitant use of ORLYNVAH and ketorolac tromethamine is contraindicated [see Drug Interactions (7.1)]

5 WARNINGS AND PRECAUTIONS

5.1 Hypersensitivity Reactions

Hypersensitivity reactions, specifically cases of angioedema, have been reported in patients treated with ORLYNVAH [see Adverse Reactions (6.1)]. Serious and occasionally fatal hypersensitivity reactions, including anaphylaxis, and serious skin reactions have been reported in patients receiving beta-lactam antibacterial drugs [see Contraindications (4)]. Before therapy with ORLYNVAH is instituted, carefully inquire about previous hypersensitivity reactions to other carbapenems, cephalosporins, penicillins, or other beta-lactams because cross- hypersensitivity among beta-lactam antibacterial drugs has been reported. Severe allergic reactions and anaphylaxis have been reported with the use of probenecid (a component of ORLYNVAH). If an allergic reaction to ORLYNVAH occurs, discontinue the drug and institute appropriate supportive measures.

5.2 Clostridioides difficile-Associated Diarrhea

Clostridioides difficile-associated diarrhea (CDAD) has been reported in users of nearly all systemic antibacterial drugs with severity ranging from mild diarrhea to fatal colitis. Treatment with antibacterial agents can alter the normal flora of the colon and may permit overgrowth of C. difficile.

C. difficile produces toxins A and B which contribute to the development of CDAD. Hypertoxin-producing strains of C. difficile cause increased morbidity and mortality, as these infections can be refractory to antibacterial therapy and may require colectomy. CDAD must be considered in all patients who present with diarrhea following antibacterial use. Careful medical history is necessary because CDAD has been reported to occur more than 2 months after the administration of antibacterial agents.

If CDAD is suspected or confirmed, ongoing antibacterial use not directed against C. difficile should be discontinued, if possible. Appropriate measures such as fluid and electrolyte management, protein supplementation, antibacterial treatment of C. difficile, and surgical evaluation should be instituted as clinically indicated.

5.3 Risk of Uric Acid Kidney Stone Development

When prescribing ORLYNVAH to patients with a history of gout, appropriate measures to reduce the risk of uric acid kidney stone development should be instituted, such as increased fluid intake and alkalization of the urine. ORLYNVAH is contraindicated in patients with known uric acid kidney stones [see Contraindications (4)].

5.4 Exacerbation of Gout

ORLYNVAH may cause exacerbation of gout. When prescribing ORLYNVAH to patients with a known history of gout, ensure appropriate therapy of gout is instituted.

5.5 Uric Acid Nephropathy in Patients at Risk for Tumor Lysis Syndrome

The probenecid component of ORLYNVAH may increase the risk of uric acid nephropathy in patients at risk for tumor lysis syndrome (TLS). When prescribing ORLYNVAH to patients with risk factors for TLS, take appropriate measures to reduce the risk.

5.6 Development of Drug-Resistant Bacteria

Prescribing ORLYNVAH in the absence of a proven or strongly suspected susceptible uUTI is unlikely to provide benefit to the patient and increases the risk of the development of drug-resistant bacteria [see Indications and Usage (1.2)].

6 ADVERSE REACTIONS

The following adverse reactions are described in greater detail in the Warnings and Precautions section.

- Hypersensitivity Reactions [see Warnings and Precautions (5.1)]
- Clostridioides difficile-Associated Diarrhea [see Warnings and Precautions (5.2)]
- Risk of Uric Acid Kidney Stone Development [see Warnings and Precautions (5.3)]
- Exacerbation of Gout [see Warnings and Precautions (5.4)]

6.1 Clinical Trials Experience

Because clinical trials are conducted under widely varying conditions, adverse reaction rates observed in the clinical trials of a drug cannot be directly compared to rates in the clinical trials of another drug and may not reflect rates observed in practice.

ORLYNVAH was evaluated in two Phase 3 controlled, multinational, randomized, double blind, double dummy clinical trials (Trial 1 and Trial 2) in adult women with uUTI. Therapy with oral ORLYNVAH tablets was administered as one tablet twice daily for 5 days [see Clinical Studies (14)]. The trials included 1932 patients treated with ORLYNVAH and 1929 patients treated with comparator antibacterial drugs (ciprofloxacin or amoxicillin/clavulanate). The median age of patients treated with ORLYNVAH was 50 years, ranging between 18 and 91 years old. Patients treated with ORLYNVAH were all female (100%), predominantly White (83%) and from the United States (83%).

Serious Adverse Reactions and Adverse Reactions Leading to Discontinuation

Serious adverse reactions occurred in 6/1932 (0.3%) of uUTI patients treated with ORLYNVAH and in 2/822 (0.2%) and 5/1107 (0.5%) of patients treated with ciprofloxacin or amoxicillin/clavulanate, respectively. Treatment discontinuation due to an adverse reaction occurred in 21/1932 (1%) of patients treated with ORLYNVAH, 8/822 (1%) of patients treated with ciprofloxacin, and 4/1107 (0.4%) of patients treated with amoxicillin/clavulanate. The most commonly reported adverse reactions leading to discontinuation of ORLYNVAH were nausea (6/1932; 0.3%), diarrhea (5/1932; 0.3%), as well as abdominal pain, gastroesophageal reflux disease, vomiting, and dizziness, each 0.2% (3/1932).

Most Common Adverse Reactions

Adverse reactions occurring at 2% or greater in patients receiving ORLYNVAH were diarrhea, nausea, vulvovaginal mycotic infection, headache, and vomiting.

Table 1 lists adverse reactions reported in ≥1% of patients receiving ORLYNVAH in the phase 3 uUTI trials (Trial 1 and Trial 2). The most common adverse reactions in patients treated with ORLYNVAH were diarrhea (10%) and nausea (4%).

Table 1. Adverse Reactions Occurring in ≥ 1% of Patients Receiving ORLYNVAH in the Uncomplicated Urinary Tract Infection Clinical Trials (Trial 1 and Trial 2)
Adverse Reaction | ORLYNVAHa N=1932 n (%) | Amoxicillin/Clavulanateb N=1107 n (%) | Ciprofloxacinc N=822 n (%)
Diarrhea^1 | 194 (10) | 45 (4) | 21 (3)
Nausea | 80 (4) | 32 (3) | 30 (4)
Vulvovaginal mycotic infection^2 | 46 (2) | 13 (1) | 7 (1)
Headache | 42 (2) | 17 (2) | 18 (2)
Vomiting | 29 (2) | 4 (0.4) | 11 (1)
Abdominal pain^3 | 22 (1) | 11 (1) | 9 (1)
a ORLYNVAH tablets (sulopenem etzadroxil 500mg / probenecid 500mg) 1 tablet twice daily for 5 days; bAmoxicillin/clavulanate tablets (875 mg /125 mg) 1 tablet twice daily for 5 days cCiprofloxacin tablets (250 mg) 1 tablet twice daily for 3 days.
^1 Diarrhea includes diarrhea and loose stools.
^2 Vulvovaginal mycotic infection includes vulvovaginal mycotic infection, vulvovaginal candidiasis, vaginal infection, fungal infection, genital infection fungal, and yeast infection.
^3Abdominal pain includes abdominal pain, abdominal pain lower, abdominal pain upper, and abdominal discomfort.

Other Adverse Reactions of ORLYNVAH

The following selected adverse reactions were reported in the ORLYNVAH-treated patients at a rate of <1% in the uUTI Trial 1 and Trial 2:

Cardiac disorders: tachycardia

Ear and labyrinth disorders: vertigo

Gastrointestinal disorders: abdominal distension, abnormal feces, constipation, dry mouth, dyspepsia, eructation, feces discolored, feces soft, flatulence, gastroesophageal reflux disease

General disorders: asthenia, fatigue, malaise, peripheral edema, pain, pyrexia

Hepatobiliary disorders: elevated transaminases, hepatomegaly

Infections and infestations: bacterial vaginosis, Candida infection, candiduria

Metabolism and nutrition disorders: polydipsia

Musculoskeletal and connective tissue disorders: arthralgia, back pain, myositis

Nervous system disorders: ageusia, dizziness, dysgeusia, dystonia, migraine, paresthesia, presyncope, somnolence, syncope

Psychiatric disorders: confusion

Renal and urinary disorders: urine odor abnormal

Reproductive system and breast disorders: perineal pain, vaginal discharge, vulvovaginal pruritus

Respiratory disorders: cough, dyspnea

Skin and subcutaneous tissue disorders: angioedema, pruritus, rash

Vascular disorders: flushing, hypertension

Adverse Reactions Occurring with Probenecid (a component of ORLYNVAH)

The following adverse reactions associated with the use of probenecid (a component of ORLYNVAH) were identified in clinical studies or postmarketing reports. Because some of these reactions were reported voluntarily from a population of uncertain size, it is not always possible to reliably estimate their frequency or establish a causal relationship to drug exposure.

Adverse reactions not observed in clinical studies of ORLYNVAH that have been observed with probenecid (a component of ORLYNVAH) include:

Gastrointestinal disorders: hepatic necrosis, anorexia, sore gums

Hematologic: aplastic anemia, leukopenia, and hemolytic anemia which in some patients could be related to genetic deficiency of glucose-6-phosphate dehydrogenase in red blood cells, anemia

Immune system disorders: anaphylaxis, urticaria

Metabolism and nutrition disorders: precipitation of acute gouty arthritis

Renal and urinary disorders: nephrotic syndrome, uric acid stones with or without hematuria, renal colic, costovertebral pain, urinary frequency

Skin and subcutaneous tissue disorders: alopecia

7 DRUG INTERACTIONS

7.1 Potential for ORLYNVAH to Affect Other Drugs

Probenecid (a component of ORLYNVAH) is an inhibitor of organic anion transporters 1 and 3 (OAT1/3) and may increase plasma concentrations of drugs that are dependent on OAT1/3 for elimination. Table 2 provides a list of established or potentially clinically significant drug interactions.

Table 2. Established and Other Potentially Clinically Significant Drug Interactions
Concomitant Drug/Drug Class | Effect on Drug Concentration | Recommendation
Ketorolac tromethamine | ↑ ketorolac tromethamine | Contraindicated
Ketoprofen | ↑ ketoprofen | Concomitant use is not recommended.
Indomethacin | ↑ indomethacin | May increase the risk of adverse reactions. Refer to drug-specific prescribing information for dosage adjustment instructions.
Naproxen | ↑ naproxen | May increase the risk of adverse reactions. Refer to drug-specific prescribing information for dosage adjustment instructions.
Methotrexate | ↑ methotrexate | If concomitant use cannot be avoided, monitor more frequently for adverse reactions associated with methotrexate as recommended in its prescribing information.
Rifampin | ↑ rifampin | Monitor more frequently for adverse reactions associated with rifampin as recommended in its prescribing information.
Lorazepam | ↑ lorazepam | Follow the recommended lorazepam dosage modifications outlined in its prescribing information.
Oral Sulfonylureas | ↑ antidiabetic | Monitor more frequently for hypoglycemia. Follow recommended sulfonylurea dosage modifications in its prescribing information.

Valproic Acid

No valproic acid dosage adjustment is recommended when used concomitantly with ORLYNVAH. No clinically significant reduction in plasma valproic acid concentrations was observed following concomitant use with ORLYNVAH [see Clinical Pharmacology (12.3)].

7.2 Potential for Other Drugs to Affect ORLYNVAH

Sulopenem is a substrate of OAT3; therefore, drugs that inhibit OAT3 may increase sulopenem plasma concentrations [see Clinical Pharmacology (12.3)]. If concomitant use with ORLYNVAH is necessary, monitor more frequently for adverse reactions associated with ORLYNVAH (e.g., diarrhea and nausea) [see Adverse Reactions (6.1)].

7.3 Drug/Laboratory Interactions

Treatment with ORLYNVAH may interfere with copper sulfate urine glucose tests, resulting in false-positive readings for glycosuria. Suspected glycosuria should be confirmed by using a test specific for glucose.

Falsely high readings for theophylline have been reported in an in vitro study, using the Schack and Waxler technique, when therapeutic concentrations of theophylline and probenecid (a component of ORLYNVAH) were added to human plasma.

8 USE IN SPECIFIC POPULATIONS

8.1 Pregnancy

Risk Summary

Sulopenem Etzadroxil

There are no available data on sulopenem etzadroxil use in pregnant women to evaluate for a drug-associated risk of major birth defects, miscarriage or adverse maternal or fetal outcomes. Sulopenem etzadroxil was orally administered during organogenesis in embryo-fetal studies in mice, rats, and rabbits. In pregnant mice, maternal toxicity and an increased litter incidence of a fetal malformation, cleft palate, was observed with an oral dose of sulopenem etzadroxil associated with plasma sulopenem exposure approximately 23 times the clinical sulopenem exposure for the maximum recommended human dose (MRHD) of 1000 mg/day sulopenem etzadroxil. In pregnant rats and rabbits, orally administered sulopenem etzadroxil was not associated with fetal malformations at any dose, but in rats, maternal toxicity and reduced fetal body weights occurred at sulopenem etzadroxil doses associated with sulopenem plasma exposures approximately 2 and 6 times, respectively, the clinical sulopenem exposure for the MRHD of sulopenem etzadroxil. In rabbits, maternal toxicity and reduced fetal body weights occurred at sulopenem etzadroxil doses associated with sulopenem plasma exposures approximately 0.1 and 0.2 times, respectively, the clinical sulopenem exposure for the MRHD of sulopenem etzadroxil.

Probenecid

Available published data over several decades of probenecid use in pregnant woman have not identified a drug-associated risk of miscarriage, major birth defects, or adverse maternal or fetal outcomes. Probenecid crosses the placental barrier and appears in cord blood.

The estimated background risk of major birth defects and miscarriage for the indicated population is unknown. All pregnancies have a background risk of birth defect, loss, or other adverse outcomes. In the U.S. general population, the estimated background risk of major birth defects and miscarriage in clinically recognized pregnancies is 2% to 4% and 15% to 20%, respectively.

Data

Animal Data

Sulopenem etzadroxil:

In an embryo-fetal development (EFD) study in mice, sulopenem etzadroxil was administered to pregnant females in oral doses of 100, 400, and 2000 mg/kg/day during the period of organogenesis from GD 6 to GD 15. Reduced fetal body weights and a fetal malformation, cleft palate, occurred with an increased fetal and litter incidence in the 2000 mg/kg/day group (approximately 23 times the clinical sulopenem exposure for the MRHD of sulopenem etzadroxil based on plasma AUC comparison). At the same dose, maternal clinical signs (rales, dyspnea, decreased motor activity) were observed, and maternal body weight gains were reduced. No maternal toxicity or fetal malformations occurred with doses ≤ 400 mg/kg/day (approximately 3 times the clinical sulopenem exposure for the MRHD of sulopenem etzadroxil based on plasma AUC comparison).

In an EFD study in rats, sulopenem etzadroxil was administered to pregnant females in oral doses of 100, 400, and 2000 mg/kg/day during the period of organogenesis from GD 6 to GD 17. Maternal body weights and food consumption were reduced in the 400 and 2000 mg/kg/day groups. No fetal malformations were observed at any sulopenem etzadroxil dose, but fetal body weights were reduced in the 2000 mg/kg/day group (approximately equal to 11 times the clinical sulopenem exposure for the MRHD of sulopenem etzadroxil based on plasma AUC comparison). The doses at which no maternal toxicity or fetal toxicity occurred were, respectively, 100 mg/kg/day and 400 mg/kg/day (less than or equal to and approximately 2 times respectively the clinical sulopenem exposure for the MRHD of sulopenem etzadroxil based on plasma AUC comparison).

In an EFD study in rabbits, sulopenem etzadroxil was administered intravenously to pregnant females in doses of 5, 15, and 50 mg/kg/day during the period of organogenesis from GD 7 to GD 19. Maternal body weight gain and food consumption were decreased in all the sulopenem etzadroxil dose groups. No fetal malformations occurred, but the number of fetal resorptions and postimplantation loss were increased and the number of viable fetuses and fetal body weights were decreased in the 15 and 50 mg/kg/day groups (approximately 0.2-times and equal to, respectively, the clinical sulopenem exposure for the MRHD of sulopenem etzadroxil based on plasma AUC comparison). The dose at which no fetal toxicity occurred was 5 mg/kg/day (approximately 0.1-times the clinical sulopenem exposure for the MRHD of sulopenem etzadroxil based on plasma AUC comparison).

In a pre- postnatal study in rats, sulopenem etzadroxil was administered by oral gavage to pregnant females from GD 6 through the lactation period to Lactation Day (LD) 20 in maternal doses of 100, 300, and 1000 mg/kg/day.

No adverse effects on the survival, growth, behavior, or reproduction of first-generation offspring occurred with any of the sulopenem etzadroxil doses up to the high dose of 1000 mg/kg/day (approximately 10-times the MRHD of sulopenem etzadroxil based on body surface area comparison).

8.2 Lactation

Risk Summary

There are no data on the presence of sulopenem etzadroxil or its metabolite in human milk, the effects on the breastfed infant, or the effects on milk production. The active metabolite of sulopenem etzadroxil, sulopenem, was present in rat milk after oral dosing of sulopenem etzadroxil to lactating female rats. When a drug is present in animal milk, it is likely that the drug will be present in human milk. Probenecid is present in human milk based on a case report. There are no reports of adverse effects in infants associated with probenecid exposure through breastmilk. There is no information on the effects of probenecid on milk production.

The developmental and health benefits of breastfeeding should be considered along with the mother’s clinical need for ORLYNVAH and any potential adverse effects on the breast-fed child from ORLYNVAH or from the underlying maternal condition.

8.4 Pediatric Use

The safety and effectiveness of ORLYNVAH in pediatric patients have not been established.

Juvenile Animal Toxicity Data

In a toxicology study with juvenile rats, sulopenem etzadroxil was orally administered from postnatal day (PND) 5 to PND 90 (85 days of dosing) in doses of 25, 75, and 225 mg/kg/day. Juvenile rats exhibited kidney toxicity including tubular epithelial degeneration and tubule concretions at doses ≥ 25 mg/kg/day (approximately 0.3 times the clinical sulopenem exposure for the MRHD of sulopenem etzadroxil based on plasma AUC comparison).

8.5 Geriatric Use

In uUTI Trial 1, there were 436 patients 65 years of age and older [see Clinical Studies (14.1)]. Of the total number of ORLYNVAH-treated patients in this study, 224 (20.2%) were 65 years of age and older, while 80 (7.2%) were 75 years of age and older. No overall differences in safety or effectiveness of ORLYNVAH were observed between patients 65 years and older and younger adult patients.

In uUTI Trial 2, there were 452 patients 65 years of age and older [see Clinical Studies (14.1)]. Of the total number of ORLYNVAH-treated patients in this study, 218 (26.2%) were 65 years of age and older, while 86 (10.3%) were 75 years of age and older. No overall differences in safety or effectiveness of ORLYNVAH were observed between patients 65 years and older and younger adult patients.

No clinically meaningful differences in the pharmacokinetics of ORLYNVAH were observed in geriatric patients compared to younger adult patients [see Clinical Pharmacology (12.3)].

No dosage adjustment based on age is required. ORLYNVAH is known to be substantially excreted by the kidney, and geriatric patients are anticipated to have reduced renal function. Recommendations for use in elderly patients should be based on renal function [see Dosage and Administration (2.2), Use in Specific Populations (8.6) and Clinical Pharmacology (12.3)].

8.6 Renal Impairment

Increases in sulopenem plasma concentrations were observed with mild, moderate and severe renal impairment; however, the available safety information does not suggest a need for dosage adjustments in these patients [see Clinical Pharmacology (12.3)]. Administration of ORLYNVAH is not recommended in patients with CrCL less than 15 mL/min and patients on hemodialysis because the pharmacokinetics of sulopenem have not been studied in this population.

10 OVERDOSAGE

There is no information on clinical signs and symptoms associated with an overdose of ORLYNVAH. No clinical information is available on the use of hemodialysis to treat ORLYNVAH overdosage.

11 DESCRIPTION

ORLYNVAH (sulopenem etzadroxil and probenecid) tablets contain sulopenem etzadroxil, a penem antibacterial drug, and probenecid, a renal tubular transport inhibitor.

The chemical name of sulopenem etzadroxil is 4-Thia-1-azabicyclo[3.2.0]hept-2-ene-2-carboxylic acid, 6-[(1R)-1- hydroxyethyl]-7-oxo-3-[[(1R,3S)- tetrahydro-1-oxido-3-thienyl]thio]-, (2-ethyl-1-oxobutoxy)methyl ester, (5R,6S)-. See Figure 1 for sulopenem etzadroxil chemical structure and chemical formula. The molecular weight of sulopenem etzadroxil is 477.61 g/mol.

Figure 1. Sulopenem Etzadroxil Chemical Structure and Formula

The chemical name for probenecid is 4-[(dipropylamino) sulfonyl] benzoic acid. See Figure 2 for probenecid chemical structure and chemical formula. The molecular weight of probenecid is 285.36 g/mol.

Figure 2. Probenecid Chemical Structure and Formula

ORLYNVAH are pink bilayer tablets for oral use containing 500 mg of sulopenem etzadroxil and 500 mg of probenecid and the following inactive ingredients: croscarmellose sodium, hydroxypropylcellulose, lactose monohydrate, magnesium stearate, and microcrystalline cellulose. The film coating contains carmine, lecithin polyvinyl alcohol, talc, titanium dioxide, and xanthan gum.

12 CLINICAL PHARMACOLOGY

12.1 Mechanism of Action

ORLYNVAH is a combination of sulopenem etzadroxil, a penem antibacterial drug [see Microbiology 12.4] and probenecid, a renal tubular transport inhibitor. Probenecid inhibits OAT3-mediated renal clearance of sulopenem, resulting in increased plasma concentrations of sulopenem.

12.2 Pharmacodynamics

Similar to other beta-lactam antimicrobial drugs, the percentage of time that unbound plasma concentrations of sulopenem exceed the sulopenem minimum inhibitory concentration (MIC) against the infecting organism has been shown to best correlate with efficacy in in vitro models of infection.

Cardiac Electrophysiology

At a concentration of 40 times or greater than that achieved after a single oral administration of ORLYNVAH, sulopenem does not prolong the QTc interval to a clinically relevant extent.

12.3 Pharmacokinetics

Sulopenem etzadroxil is a prodrug [see Microbiology 12.4]. The pharmacokinetics of sulopenem and probenecid were characterized in healthy subjects following single oral administration of ORLYNVAH (500 mg sulopenem etzadroxil and 500 mg probenecid). Pharmacokinetic parameters are presented in Table 3 as mean [coefficient of variation (%CV)] unless otherwise specified.

Table 3. Pharmacokinetics of Sulopenem and Probenecid in Plasma after Single Oral Dose Administration of ORLYNVAH in Healthy Subjects
Parameter |  | Sulopenem |  | Probenecid
 |  | Fasted | Feda | Fasted | Feda
General Information
Exposureb
Cmax |  | 1.84 (39.1) | 2.66 (43.6) | 41.2 (38.2) | 30.4 (30.9)
AUC0-inf |  | 4.85 (25.3) | 7.41 (22.7) | 255 (35.6) | 237 (35.2)
Dose Proportionalityb |  | Dose Proportional |  | unknown
Accumulation |  | None |  | unknown
Absorption
Bioavailability |  | 40% | 64% | unknown
Tmax Median (range) |  | 1.0 (0.5 to 3.0) | 2.0 (1.0 -3.0) | 3.0 (1.0 – 10.0) | 2.0 (1.50 to 6.0)
Effect of Food
High fat meala (Fed:Fasted ratio) | Cmax | Increased 45% |  | Decreased 27%
 | AUC0-inf | Increased 48% |  | Decreased 8%
Distribution
Apparent Volume of Distribution (Liters) (mean (SD)) |  | 134 (51.36) | 92.09 (33.43) | 8.81 (3.91) | 11.94 (3.46)
Protein Bindingc |  | 11% |  | Unknown
Elimination
Half-Life (hours) (mean (SD)) |  | 1.18 (0.24) | 1.28 (0.49) | 2.93 (0.83) | 3.83 (0.50)
Apparent Clearance (L/hour) (mean (SD)) |  | 77.6 (19.77) | 50.55 (11.60) | 2.06 (0.70) | 2.22 (0.76)
Metabolism
Primary Pathway |  | Sulopenem etzadroxil is hydrolyzed by esterases to active sulopenem then further metabolized by hydrolysis followed by dehydrogenation |  | unknown
Major Metabolites |  | M1a and M1bd (inactive) |  | unknown
Excretione
Feces |  | 44.3% (26.9% unchanged) |  | unknown
Urine |  | 40.8% (3.1% unchanged) |  | unknown
Abbreviations: Cmax = maximum plasma concentration; AUC= area under the time concentration curve; Tmax = time to peak concentration
a A high fat meal is 800-1000 calories, approximately 50% of total calories from fat
b No clinically significant sulopenem divergence from dose-proportionally was observed over a dose range of 400 mg to 2000 mg (0.8 to 4 times the approved recommended sulopenem etzadroxil dosage)
c Independent of concentration over a range of 1 to 100 µg/mL
d Sulopenem, M1a and M1b, accounted for 32%, 21.8% and 43.6% of circulating radioactivity, respectively
e After a single oral dose of radiolabeled sulopenem etzadroxil 2000 mg healthy adult subjects

Specific Populations

No clinically significant differences in the pharmacokinetics of sulopenem were observed based on age, sex or weight. The effect of hepatic impairment on sulopenem pharmacokinetics is unknown.

Patients with Renal Impairment

Sulopenem mean plasma AUC0-inf increased by 2-fold in patients with mild (CrCL 60 to 89 mL/min), estimated by Cockcroft-Gault equation), by 3-fold in patients with moderate (CrCL 30 to 59 mL/min) and by 7.4-fold in patients with severe (CrCL15 to 29 mL/min) renal impairment following administration of 1000 mg oral sulopenem etzadroxil (not a recommended dosing regimen) [see Dosage and Administration (2.1)]. The effect of kidney failure (CrCL<15 mL/min) or hemodialysis on sulopenem pharmacokinetics is unknown.

Drug Interaction Studies

Clinical Studies

Effect of Other Drugs on the Pharmacokinetics of ORLYNVAH:

No clinically significant differences in the pharmacokinetics of sulopenem were observed when ORLYNVAH was administered concomitantly with oral itraconazole (P-gp inhibitor), pantoprazole (gastric-acid reducing agent) or aluminum hydroxide (gastric acid-reducing agent).

No clinically significant differences in the pharmacokinetics of valproic acid were observed when used concomitantly with ORLYNVAH. Although there are case reports in the published literature that suggest concomitant use of carbapenems result in a reduction in valproic acid concentrations, the probenecid component of ORLYNVAH appears to counteract any potential effect of sulopenem on valproic acid [see Drug Interactions (7.1)].

Effect of ORLYNVAH on the Pharmacokinetics of Other Drugs:

Coadministration of multiple doses of 500 mg sulopenem etzadroxil with valproic acid decreased valproic acid plasma AUC0-tau and Cmax by approximately 25% and 19%, respectively. However, no clinically significant differences in the pharmacokinetics of valproic acid were observed when administered concomitantly with ORLYNVAH. AUC0-tau and Cmax decreased by 8.4% and 7%, respectively, with concomitant administration of ORLYNVAH.

In Vitro Studies

CYP450 Enzymes:

Sulopenem does not inhibit CYP1A2, CYP2B6, CYP2C8, CYP2C9, CYP2C19, CYP2D6 or CYP3A or induce CYP1A2, CYP2B6, or CYP3A4/5.

Transporter Systems:

Sulopenem is a substrate of OAT3 and does not inhibit BCRP, P-gp, BSEP, MATE1, MATE2K, OAT1, OAT3, OATP1B1, OATP1B3, OCT1, or OCT2. Probenecid is a substrate for BCRP and an inhibitor of OAT1/3, but does not inhibit BSEP, P-gp, or MRP2.

12.4 Microbiology

Mechanism of Action

Sulopenem etzadroxil is a prodrug that is hydrolyzed to the active drug sulopenem after oral administration. Sulopenem has in vitro activity against gram-positive and gram-negative aerobic and anaerobic bacteria. The bactericidal activity of sulopenem results from the inhibition of cell wall synthesis and is mediated through sulopenem binding to penicillin binding proteins (PBPs). In Escherichia coli, sulopenem demonstrated binding affinity for PBPs in the following order: PBP2 > PBP1A > PBP1B > PBP4 > PBP3 > PBP5/6.

Resistance

Resistance to sulopenem is caused by certain extended spectrum beta-lactamases (ESBLs) including carbapenemases, alteration of PBPs, over expression of efflux pumps and loss of outer membrane porins. Sulopenem demonstrated activity against Enterobacterales in the presence of certain beta-lactamases and ESBLs, e.g., AmpC, CTX-M, TEM, SHV. Sulopenem resistant mutants were selected in vitro at a frequency of 1×10^-^8.

Interaction with Other Antimicrobials

In vitro studies with sulopenem did not demonstrate antagonism with any of the following antimicrobials: amoxicillin, aztreonam, ceftriaxone, doxycycline, gentamicin, levofloxacin, nitrofurantoin, vancomycin or trimethoprim-sulfamethoxazole. The clinical significance of these in vitro findings is unknown.

Antimicrobial Activity

Sulopenem has been shown to be active against most isolates of the following microorganisms, both in vitro and in clinical infections [see Indications and Usage (1.1)]:

Gram-negative bacteria

Escherichia coli

Klebsiella pneumoniae

Proteus mirabilis

The following in vitro data are available, but their clinical significance is unknown. At least 90 percent of the following bacteria exhibit an in vitro minimum inhibitory concentration (MIC) less than or equal to the susceptible breakpoint for sulopenem against isolates of similar genus or organism group. However, the efficacy of sulopenem in treating clinical infections caused by these bacteria has not been established in adequate and well-controlled clinical trials.

Gram-positive bacteria

Staphylococcus saprophyticus

Streptococcus agalactiae

Gram-negative bacteria

Citrobacter freundii

Citrobacter koseri

Enterobacter cloacae species Complex

Klebsiella aerogenes

Klebsiella oxytoca

Proteus vulgaris

Providencia alcalifaciens

Providencia stuartii

Susceptibility Testing

For specific information regarding susceptibility test interpretive criteria, and associated test methods and quality control standards recognized by FDA for this drug, please see https://www.fda.gov/STIC.

13 NONCLINICAL TOXICOLOGY

13.1 Carcinogenesis, Mutagenesis, Impairment of Fertility

Carcinogenesis

Carcinogenicity studies in animals have not been conducted with ORLYNVAH.

Mutagenesis

Sulopenem Etzadroxil

Sulopenem etzadroxil was negative for mutations in an in vitro Ames assay with and without metabolic activation but positive for chromosome aberrations with and without metabolic activation in vitro in peripheral human lymphocytes and Chinese hamster ovary cells. In vivo, sulopenem etzadroxil was negative for genetic toxicity in a bone marrow micronucleus assay in rats.

Sulopenem

Sulopenem did not induce mutations in a reverse mutation assay in bacterial cells with and without metabolic activation or in a CHO HGPRT mammalian cell mutation assay with and without metabolic activation. Sulopenem was positive for chromosome aberrations in vitro in V79 Chinese hamster lung cells, but negative for genetic toxicity in vivo in bone marrow micronucleus assays in mice and rats.

Probenecid

Probenecid was shown to be negative for mutagenicity in an in vitro Ames assay with and without metabolic activation and negative for chromosome aberrations in an in vitro chromosome aberration assay in Chinese hamster ovary cells with and without metabolic activation.

Impairment of Fertility

Sulopenem etzadroxil

Male and female fertility and early embryonic development were examined in rats (20/sex/group) orally administered sulopenem etzadroxil in daily doses of 100, 400, or 2000 mg/kg beginning 28 days prior to mating and throughout the mating period in males and for 14 days before mating, throughout the mating period, and until Gestation Day (GD) 7 in females. There were no treatment-related effects on estrous cycle length, mating and fertility rates, implantation, conceptus viability, sperm concentration and motility, or accessory male sex glands weights. No adverse effects on male and female fertility or early embryonic development in female rats were observed at doses up to 2000 mg/kg/day (approximately 10- and 12-times in male and female rats, respectively, the clinical sulopenem exposure for the MRHD of sulopenem etzadroxil based on plasma AUC comparison).

Probenecid

No fertility studies have been conducted with probenecid.

13.2 Animal Toxicology and/or Pharmacology

In a toxicology study in monkeys, daily oral administration of sulopenem etzadroxil for 30 days was associated with reduced red blood cell counts and increased reticulocytes at doses of ≥ 400 mg/kg/day (approximately 6-times the clinical sulopenem exposure for the MRHD of sulopenem etzadroxil based on AUC comparison). In the same animals, positive Coomb’s assay results demonstrated positive reactions for polyspecific anti-human globulin and anti-IgG suggesting red cell loss may have been mediated by antibodies. Similar findings were also observed in toxicology studies with sulopenem administered intravenously to monkeys.

14 CLINICAL STUDIES

14.1 Uncomplicated Urinary Tract Infections

Trial 1

A total of 2222 adult women with uncomplicated urinary tract infections (uUTI) were randomized and 2214 received trial medications in a randomized, double-blind clinical trial (Trial 1) (NCT05584657) comparing oral ORLYNVAH (sulopenem etzadroxil 500 mg and probenecid 500 mg) twice daily for 5 days to oral amoxicillin/clavulanate 875 mg/125 mg twice daily for 5 days.

The microbiological modified intent-to-treat (micro-MITT) population, which included all patients who had at least one uropathogen isolated at baseline (≥10^5 CFU/mL) and received at least one dose of study drug, consisted of 990 patients; the median age was 51 years and median weight was 73.5 kg. Patients were enrolled only from the United States. Patients were Caucasian (79.7%), African American (17.0%) or of another race (3.3%).

Composite response (combined microbiological response and clinical cure rates) was determined by comparing the response rate of ORLYNVAH to amoxicillin/clavulanate at the TOC visit (12 days after randomization) in the micro-MITT population as well as in two sub-populations: a) micro-MITTS (micro-MITT population with baseline pathogens susceptible to amoxicillin/clavulanate, MIC ≤8/4 g/mL) and b) micro-MITTR (micro-MITT population with baseline pathogens non-susceptible to amoxicillin/clavulanate, MIC ≥16/8 g/mL). Clinical cure was defined as the resolution of patient-reported uUTI symptoms and no new uUTI symptoms. Microbiological response was defined as a reduction of all baseline uropathogens to less than 10^3 CFU/mL in the urine.

ORLYNVAH demonstrated efficacy in the micro-MITTS population. The micro-MITTR population was small (N=67) and had insufficient power to draw conclusions regarding efficacy (Table 4).

Table 4. Composite Response^1 at the Test of Cure Visit in Patients with uUTI, Trial 1
Study Population | ORLYNVAHa n/N (%) | Amoxicillin/ clavulanateb n/N (%) | Treatment Difference (95% CI) c
micro-MITTSd Population
Composite response | 296/480 (61.7) | 243/442 (55.0) | 6.7 (0.3, 13.0)
Clinical cure | 371/480 (77.3) | 339/442 (76.7) | 0.6 (-4.8, 6.1)
Microbiological response | 361/480 (75.2) | 295/442 (66.7) | 8.5 (2.6, 14.3)
micro-MITTRe population
Composite response | 22/42 (52.4) | 17/25 (68.0) | -15.6 (-37.5, 9.1)
Clinical cure | 26/42 (61.9) | 18/25 (72.0) | -10.1 (-31.5, 14.0)
Microbiological response | 29/42 (69.0) | 20/25 (80.0) | -11.0 (-30.7, 12.0)
^1 Combined Clinical and Microbiological Success; a 500 mg/500 mg orally twice daily for 5 days; b 875 mg/125 mg orally twice daily for 5 days; c The 95% confidence interval (CI) was calculated using the unstratified Miettinen and Nurminen method; d microbiological modified intent-to-treat population with baseline pathogens susceptible (MIC ≤8/4 g/mL) to amoxicillin/clavulanate; e microbiological modified intent-to-treat population with baseline pathogens nonsusceptible (MIC ≥16/8 g/mL) to amoxicillin/clavulanate.

Composite response rates by pathogen are presented in Table 5.

Table 5. Composite Response Rate at Test of Cure by Baseline Pathogen from Patients with uUTI, Trial 1
Study Population | ORLYNVAHa n/N (%) | Amoxicillin/clavulanateb n/N (%)
micro-MITTS Population
Escherichia coli | 251/400 (62.8) | 210/374 (56.1)
Klebsiella pneumoniae | 31/57 (54.4) | 22/50 (44.0)
Proteus mirabilis | 5/13 (38.5) | 6/13 (46.2)
micro-MITTR Population
Escherichia coli | 12/23 (52.2) | 9/12 (75.0)
Klebsiella pneumoniae | 0 | 0
Proteus mirabilis | 0 | 0

a 500 mg/500 mg orally twice daily for 5 days; b 875 mg /125 mg orally twice daily for 5 days

Trial 2

A total of 1660 adult women with uUTI were randomized and received trial medications in a multinational randomized, double-blind clinical trial (Trial 2) (NCT03354598) comparing oral ORLYNVAH (sulopenem etzadroxil 500 mg and probenecid 500 mg) twice daily for 5 days to oral ciprofloxacin 250 mg twice daily for 3 days. The micro-MITT population, which included all patients who had at least one uropathogen isolated at baseline (≥10^5 CFU/mL), consisted of 1105 patients; the median age was 53 years; median weight in the randomized population was 70.4 kg. Patients were enrolled from the United States (55%) and Eastern Europe (45%). Patients were Caucasian (90%), African American (9%) or of other races (1%).

Composite response (combined microbiological response and clinical cure) was determined by comparing the response rate of ORLYNVAH to ciprofloxacin at the TOC visit (12 days after randomization) in two primary populations: micro-MITTS (micro-MITT population with baseline pathogens susceptible to ciprofloxacin, MIC ≤1 g/mL) and micro-MITTR (micro-MITT population with baseline pathogens non-susceptible to ciprofloxacin, MIC ≥2 g/mL). Clinical cure was defined as the resolution of patient-reported uUTI symptoms and no new uUTI symptoms. Microbiological response was defined as a reduction of all baseline uropathogens to less than 10^3 CFU/mL in the urine.

ORLYNVAH demonstrated efficacy in the micro-MITTR population but did not demonstrate efficacy in the micro-MITTS population (Table 6).

Table 6. Composite Response^1 at the Test of Cure Visit in Patients with uUTI, Trial 2
Study Population | ORLYNVAHa n/N (%) | Ciprofloxacinb n/N (%) | Treatment Difference (95% CI) c | P valued
micro-MITTRe Population
Composite response | 78/162 (48.1) | 49/149 (32.9) | 15.3 (4.3, 25.8) | 0.006
Clinical cure | 136/162 (84.0) | 96/149 (64.4) | 19.5 (10.0, 29.0)
Microbiological response | 92/162 (56.8) | 66/149 (44.3) | 12.5 (1.4, 23.3)
micro-MITTSf Population
Composite response | 227/376 (60.4) | 300/418 (71.8) | -11.4 (-17.9, -4.8)
Clinical cure | 305/376 (81.1) | 351/418 (84.0) | -2.9 (-8.2, 2.4)
Microbiological response | 262/376 (69.7) | 336/418 (80.4) | -10.7 (-16.7, -4.7)
^1Combined Clinical Cure and Microbiological Response; a 500 mg/500 mg orally twice daily for 5 days; b 250 mg PO twice daily for 3 days; c The 95% confidence interval (CI) was calculated using the unstratified Miettinen and Nurminen method; d The P value was calculated using Cochran–Mantel–Haenszel test; e microbiological modified intent-to-treat population with baseline pathogens nonsusceptible (MIC ≥2 g/mL) to ciprofloxacin; f microbiological modified intent-to-treat population with baseline pathogens susceptible (MIC ≤1 g/mL) to ciprofloxacin

Composite response rates by pathogen are presented in Table 7.

Table 7. Composite Response Rate at Test of Cure by Baseline Pathogen from uUTI Trial 2
 | ORLYNVAHa n/N (%) | Ciprofloxacinb n/N (%)
micro-MITTR Population
Escherichia coli | 63/141 (44.7) | 41/131 (31.3)
Klebsiella pneumoniae | 9/15 (60.0) | 7/14 (50.0)
Proteus mirabilis | 8/9 (88.9) | 3/6 (50.0)
micro-MITTS Population
Escherichia coli | 187/316 (59.2) | 244/348 (70.1)
Klebsiella pneumoniae | 23/37 (62.2) | 24/35 (68.6)
Proteus mirabilis | 5/9 (55.6) | 10/11 (90.9)

a 500 mg/500 mg orally twice daily for 5 days; b 250 mg PO twice daily for 3 days

14.2 Complicated Urinary Tract Infections - Lack of Efficacy

ORLYNVAH is not indicated for the treatment of complicated urinary tract infections. Trial 3 (NCT03357614) was a phase 3, multi-center, double-blind, randomized trial designed to compare the efficacy, tolerability, and safety of IV sulopenem followed by oral sulopenem etzadroxil and probenecid with that of IV ertapenem followed by oral ciprofloxacin or amoxicillin/clavulanate for the treatment of complicated urinary tract infections (cUTI). Trial 3 did not demonstrate the efficacy of sulopenem IV followed by oral sulopenem etzadroxil and probenecid for the primary endpoint of composite response (combined clinical and microbiologic response) in the microbiologic modified intent-to-treat (micro-MITT) population at the test-of-cure visit on Day 21 [see Indications and Usage (1.1)].

14.3 Complicated Intra-abdominal Infections - Lack of Efficacy

ORLYNVAH is not indicated for the treatment of complicated intra-abdominal infections. Trial 4 (NCT03358576) was a phase 3, multi-center, double-blind, randomized trial designed to compare the efficacy, tolerability, and safety of IV sulopenem followed by oral sulopenem etzadroxil and probenecid with that of IV ertapenem followed by oral ciprofloxacin and metronidazole or amoxicillin/clavulanate for the treatment of complicated intra-abdominal infections (cIAI). Trial 4 did not demonstrate the efficacy of IV sulopenem followed by oral sulopenem etzadroxil and probenecid for the primary endpoint of clinical response in the micro-MITT at the test-of-cure visit on Day 28 [see Indications and Usage (1.1)].

16 HOW SUPPLIED/STORAGE AND HANDLING

16.1 How Supplied

ORLYNVAH tablets are supplied as pink, oval-shaped, film-coated, fixed-dose, bilayer combination tablets debossed with SULO on one side and plain on the other side, containing 500 mg of sulopenem etzadroxil and 500 mg of probenecid.

They are supplied as follows:

Bottles of 10 tablets with child-resistant caps (NDC 81153-100-01)

16.2 Storage and Handling

Store ORLYNVAH tablets at 20°C to 25°C (68°F to 77°F); excursions permitted to 15°C to 30°C (59°F to 86°F) [see USP Controlled Room temperature].

17 PATIENT COUNSELING INFORMATION

Allergic Reactions

Advise patients that allergic reactions, including serious allergic reactions, could occur, and that serious allergic reactions require immediate treatment. Patients should inform their healthcare provider about any previous hypersensitivity reactions to ORLYNVAH, other beta-lactam antibacterial drugs or probenecid [see Warnings and Precautions (5.1)].

Diarrhea

Advise patients that diarrhea is a common problem caused by antibacterial drugs, including ORLYNVAH, and usually resolves when the drug is discontinued. Sometimes, frequent watery or bloody diarrhea may occur and may be a sign of a more serious intestinal infection. If severe watery or bloody diarrhea develops, patients should contact their healthcare provider [see Warnings and Precautions (5.2) and Adverse Reactions (6.1)].

Antibacterial Resistance

Patients should be counseled that ORLYNVAH should only be used to treat proven or strongly suspected susceptible uUTI. Antibacterial drugs do not treat viral infections (e.g., the common cold). When ORLYNVAH is prescribed to treat proven or strongly suspected susceptible uUTI, patients should be told that although it is common to feel better early in the course of therapy, ORLYNVAH should be taken exactly as directed. Skipping doses or not completing the full course of therapy may (1) decrease the effectiveness of the immediate treatment, and (2) increase the likelihood that bacteria will develop resistance and will not be treatable by ORLYNVAH or other antibacterial drugs in the future [see Warnings and Precautions (5.5)].

Ketoprofen

Advise patients that concomitant use of ketoprofen with ORLYNVAH is not recommended [see Drug Interactions (7.1)].

Manufactured for: Iterum Therapeutics U.S. Limited, Chicago, IL 60606

US Patent Numbers: Available online at https://www.iterumtx.com/

ORLYNVAHTM is a registered trademark of Iterum Therapeutics

PRINCIPAL DISPLAY PANAL

NDC 81153-100-01
Rx Only
Orlynvah™
(sulopenem etzadroxil
and probenecid) tablets
500 mg/500 mg
10 Tablets